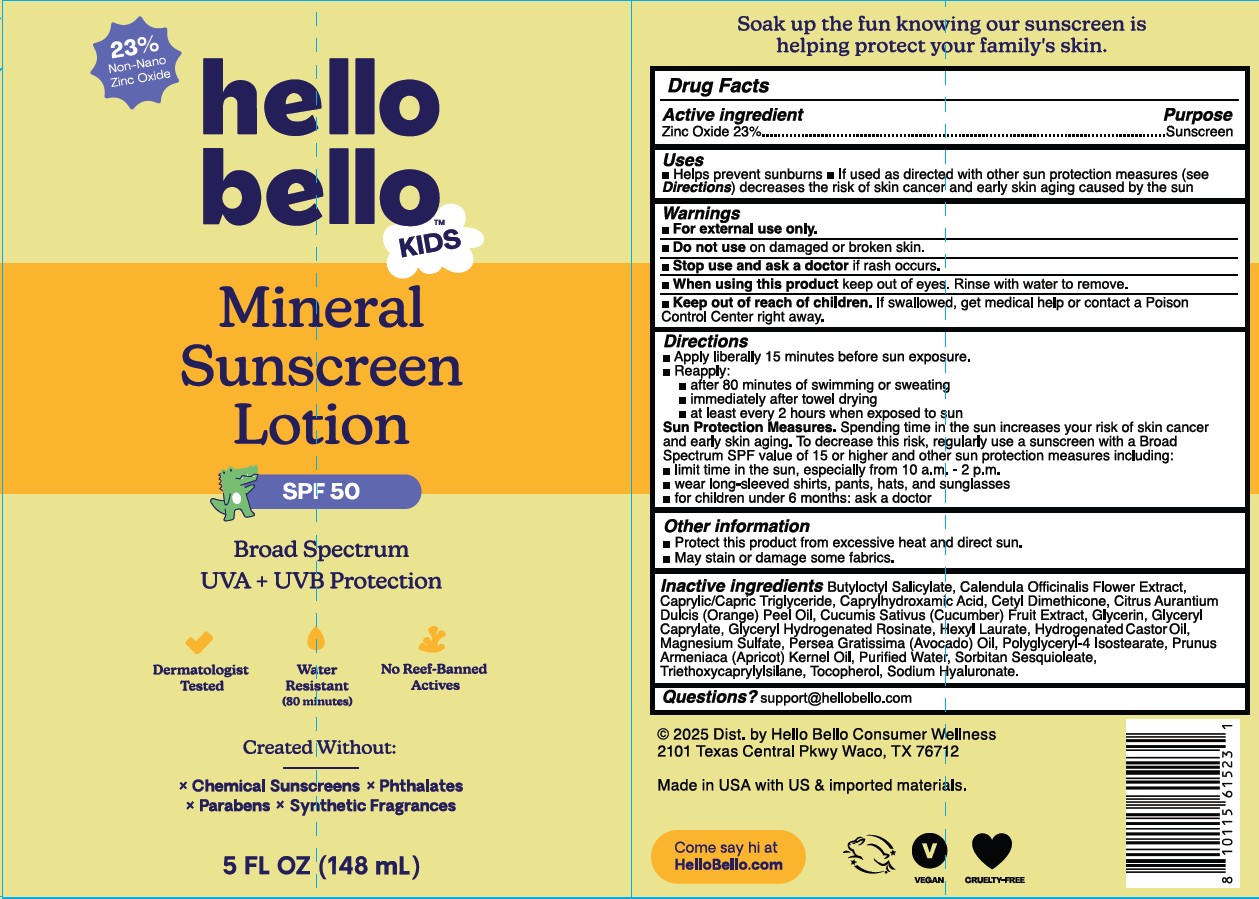 DRUG LABEL: Hello Bello Kids Mineral Sunscreen
NDC: 73418-110 | Form: LOTION
Manufacturer: Hello Bello
Category: otc | Type: HUMAN OTC DRUG LABEL
Date: 20251029

ACTIVE INGREDIENTS: ZINC OXIDE 23 mg/1 g
INACTIVE INGREDIENTS: CALENDULA OFFICINALIS FLOWER; CETYL DIMETHICONE 25; GLYCERIN; CITRUS AURANTIUM AMARA (BITTER ORANGE) PEEL OIL; CAPRYLHYDROXAMIC ACID; AQUA; TRIETHOXYCAPRYLYLSILANE; POLYGLYCERYL-4 ISOSTEARATE; GLYCERYL CAPRYLATE; CUCUMIS SATIVUS (CUCUMBER) JUICE; HYDROGENATED CASTOR OIL; MAGNESIUM SULFATE; SORBITAN SESQUIOLEATE; SODIUM HYALURONATE; BUTYLOCTYL SALICYLATE; CAPRYLIC/CAPRIC ACID; GLYCEROL ESTER OF HYDROGENATED ROSIN; .ALPHA.-TOCOPHEROL, DL-; APRICOT KERNEL OIL; HEXYL LAURATE; AVOCADO OIL

Hello Bello Kids SPF 50 Mineral Sunscreen Lotion

Other Information

Protect this product from excessive heat and direct sun

May stain some fabrics

Active Ingredients

Zinc Oxide 23%

Purpose

Sunscreen

Uses

Helps prevent sunburn
If used as directed with other sun protection measures (see Directions), decreases the risk of skin cancer and early skin aging caused by the sun

Directions

Shake well before use

Apply liberally and spread evenly by hand 15 minutes before sun exposure

Reapply:

after 80 minutes of swimming or sweating immediately after towel use
at least every 2 hours

Sun Protection Measures

Spending time in the sun can increase your risk of skin cancer and early skin aging. To decrease this risk, regularly use sunscreen with a Broad Spectrum SPF value of 15 or higher and other sun protection measures including:

Limiting time in the sun, especially from 10a.m. - 2p.m.
Wearing long-sleeved shirts, pants, hats and sunglasses

Children under six months: Ask a doctor

Other Information

Protect this product from excessive heat and direct sun

May stain some fabrics

Inactive Ingredients

Butyloctyl Salicylate

Questions?

Support@HelloBello.com